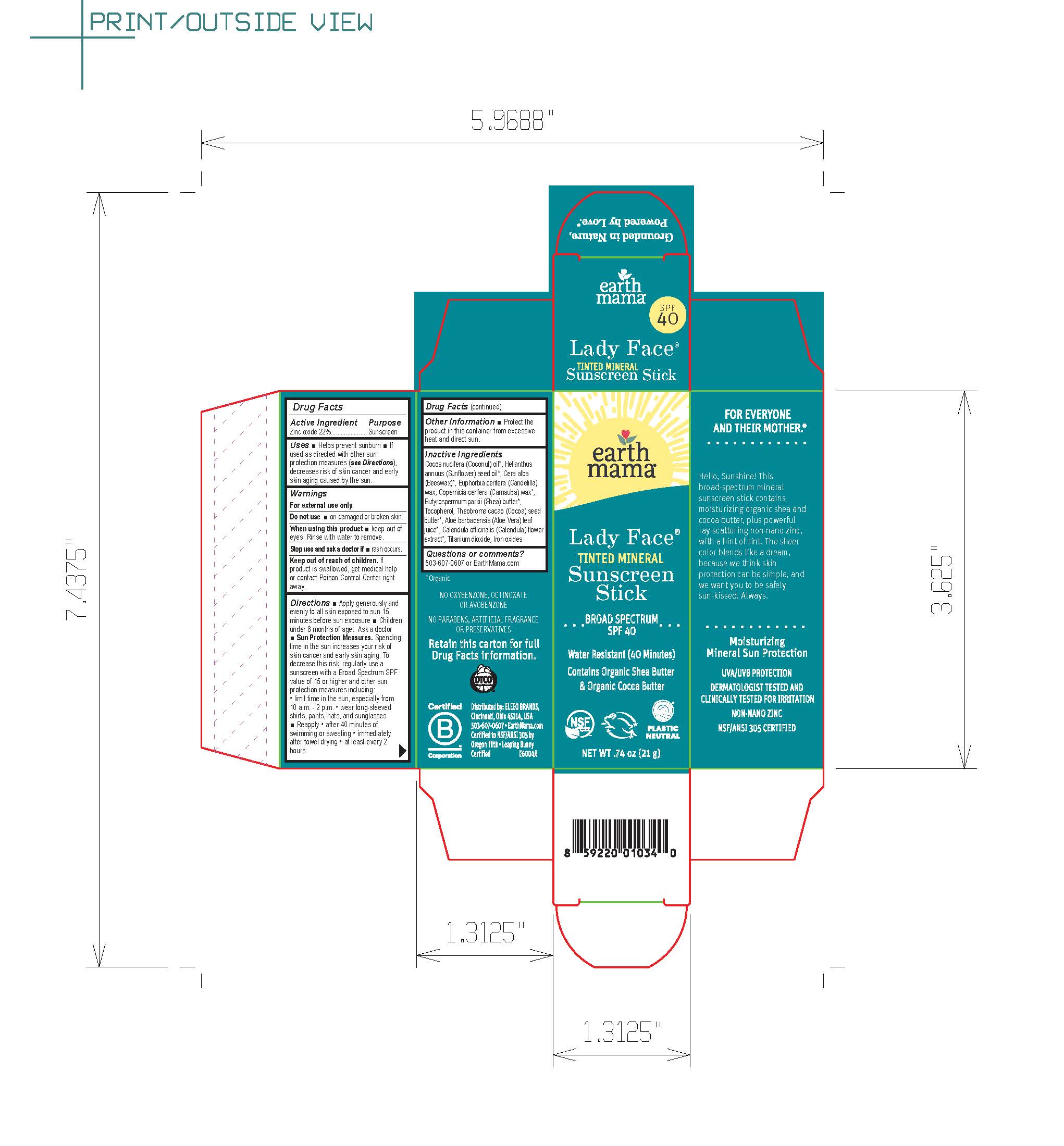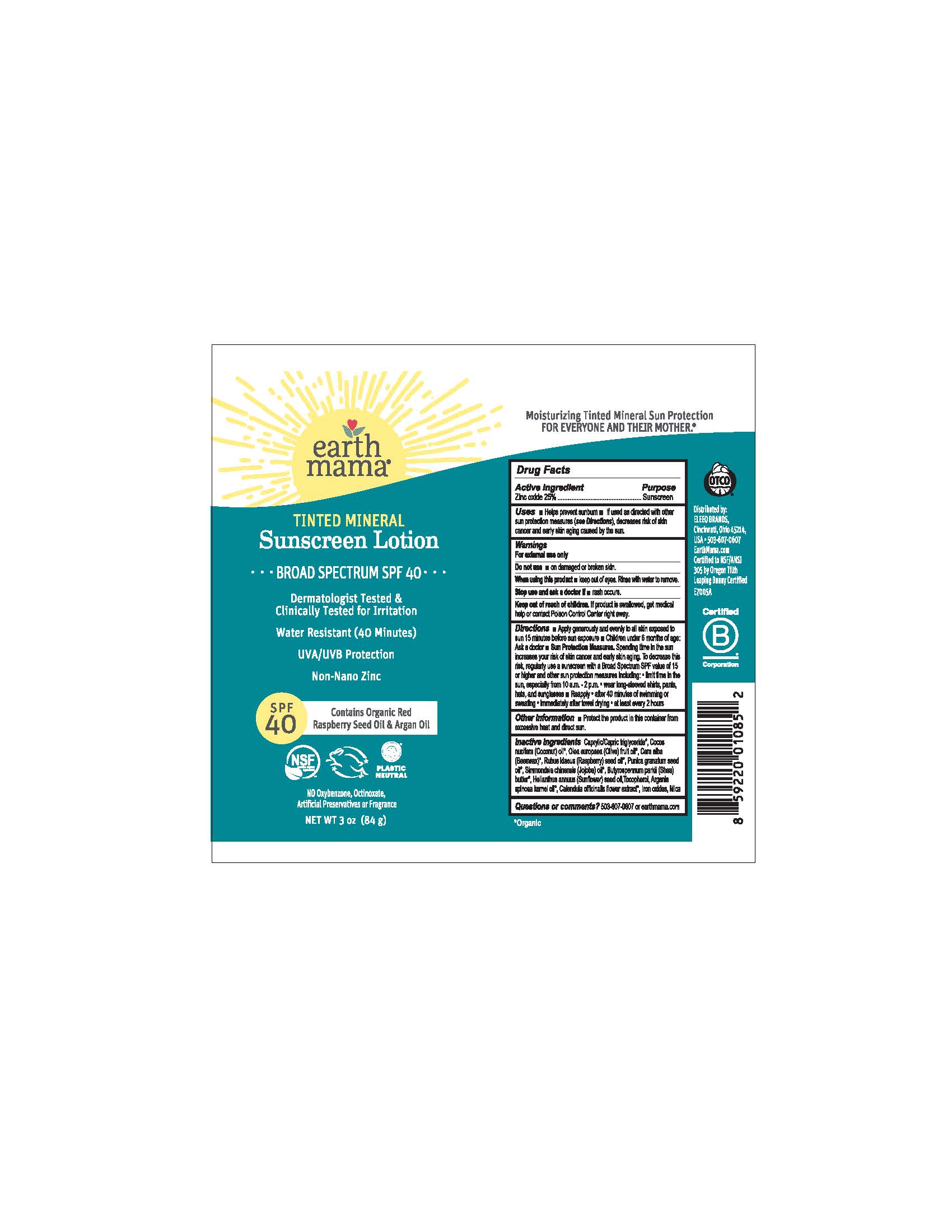 DRUG LABEL: Earth Mama Lady Face Tinted Mineral Sunscreen Stick SPF 40
NDC: 79747-149 | Form: STICK
Manufacturer: Eleeo Brands LLC
Category: otc | Type: HUMAN OTC DRUG LABEL
Date: 20250813

ACTIVE INGREDIENTS: ZINC OXIDE 22 g/100 g
INACTIVE INGREDIENTS: COCONUT OIL; SUNFLOWER OIL; YELLOW WAX; CANDELILLA WAX; CARNAUBA WAX; SHEA BUTTER; TOCOPHEROL; COCOA BUTTER; ALOE VERA LEAF; CALENDULA OFFICINALIS FLOWER; TITANIUM DIOXIDE; FERRIC OXIDE RED

Earth Mama Lady Face Mineral Sunscreen - Light/Medium Tint Broad Spectrum SPF 40

Active Ingredient

Zinc Oxide 22%

Purpose

Sunscreen

Uses

• Helps prevent sunburn • If used as directed with other sun protection measures (see Directions), decreases risk of skin cancer and early skin aging caused by the sun.

Warnings

For external use only

Do not use• on damaged or broken skin

When using this product• keep out of eyes. Rinse with water to remove.

Stop use and ask a doctor if• rash occurs.

Keep out of reach of children. If product is swallowed, get medical help or contact Poison Control Center right away.

Directions

• Apply generously and evenly to all skin exposed to sun 15 minutes before sun exposure • Children under 6 months of age: Ask a doctor
• Sun Protection Measures.Spending time in the sun increases your risk of skin cancer and early skin aging. To decrease this risk, regularly use a sunscreen with a Broad Spectrum SPF value of 15 or higher and other sun protection measures including: • limit time in the sun, especially from 10 a.m. - 2 p.m. • wear long-sleeved shirts, pants, hats, and sunglasses
• Reapply • after 40 minutes of swimming or sweating • immediately after towel drying • at least every 2 hours

Other Information

• Protect the product in this container from excessive heat and direct sun

Inactive Ingredients

Cocos Nucifera (Coconut) Oil*, Helianthus Annuus (Sunflower) Seed Oil*, Beeswax*, Euphorbia Cerifera (Candelilla) Wax, Copernicia Cerifera (Carnauba) Wax*, Butyrospermum Parkii (Shea) Butter*, Tocopherol, Theobroma Cacao (Cocoa) Seed Butter*, Aloe Barbadensis (Aloe Vera) Leaf Juice*, Calendula Officinalis (Calendula) Flower Extract*, Titanium Dioxide, Iron Oxides.

*Organic

Questions or comments?

503-607-0607 or EarthMama.com

MOISTURIZING TINTED FACE STICK

Water Resistant (40 Minutes)

NSF
contains organic ingredients

PLASTIC NEUTRAL

FOR EVERYONE AND THEIR MOTHER.®

Hello, Sunshine! This broad-spectrum mineral sunscreen stick is formulated to protect your skin without concerning chemicals - and contains moisturizing organic shea and cocoa butter, plus powerful, ray-scattering non-nano zinc. It's tinted with sheer color that blends like a dream and blocks blue light from digital screens. Because we think skin protection can be simple, and we went you to be safely sun-kissed. Always.

Moisturizing Mineral Sun Protection

UVA/UVB Protection

DERMATOLOGIST TESTED AND CLINICALLY TESTED FOR IRRITATION

NON-NANO ZINC

REEF-FRIENDLY

NO OXYBENZONE, OCTINOXATE OR AVOBENZONE

NO PARABENS, ARTIFICIAL FRAGRANCE OR PRESERVATIVES

Retain this carton for full Drug Facts information.

Distributed by Earth Mama Angel Baby®LLC

9866 SE Empire Ct. • Clackamas, OR 97015 USA
Certified to NSF/ANSI 305 by Oregon Tilth
Leaping Bunny Certified

Grounded in Nature, Powered by Love.®